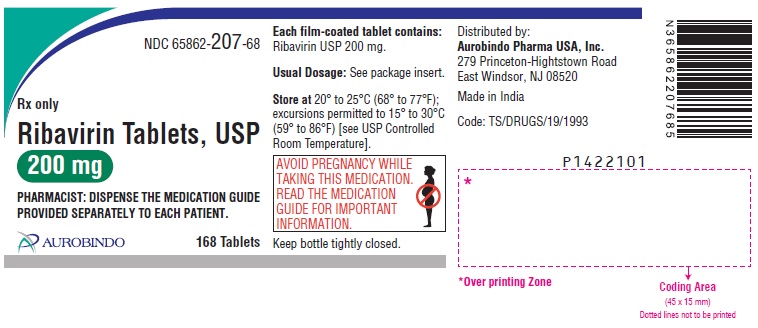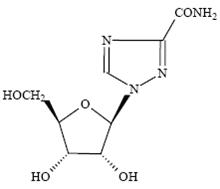 DRUG LABEL: Ribavirin
NDC: 65862-207 | Form: TABLET, FILM COATED
Manufacturer: Aurobindo Pharma Limited
Category: prescription | Type: Human Prescription Drug Label
Date: 20240206

ACTIVE INGREDIENTS: RIBAVIRIN 200 mg/1 1
INACTIVE INGREDIENTS: MICROCRYSTALLINE CELLULOSE; STARCH, CORN; SODIUM STARCH GLYCOLATE TYPE A POTATO; POVIDONE K30; SILICON DIOXIDE; MAGNESIUM STEARATE; ETHYLCELLULOSE, UNSPECIFIED; TRIACETIN; HYPROMELLOSE 2910 (15 MPA.S); FERRIC OXIDE RED; TITANIUM DIOXIDE; FERRIC OXIDE YELLOW

HIGHLIGHTS OF PRESCRIBING INFORMATION

These highlights do not include all the information needed to use RIBAVIRIN TABLETS safely and effectively. See full prescribing information for RIBAVIRIN TABLETS.
RIBAVIRIN tablets, for oral use
Initial U.S. Approval: 2002

WARNING: RISK OF SERIOUS DISORDERS AND RIBAVIRIN-ASSOCIATED EFFECTS

See full prescribing information for complete boxed warning.

- Ribavirin monotherapy, including ribavirin, is not effective for the treatment of chronic hepatitis C virus infection (Boxed Warning).
- The hemolytic anemia associated with ribavirin therapy may result in worsening of cardiac disease and lead to fatal and nonfatal myocardial infarctions. Patients with a history of significant or unstable cardiac disease should not be treated with ribavirin (2.3, 5.2, 6.1).
- Significant teratogenic and embryocidal effects have been demonstrated in all animal species exposed to ribavirin. Therefore, ribavirin is contraindicated in women who are pregnant and in the male partners of women who are pregnant. Extreme care must be taken to avoid pregnancy during therapy and for 6 months after completion of treatment in both female patients and in female partners of male patients who are taking ribavirin therapy (4, 5.1, 8.1).

1 INDICATIONS AND USAGE

Ribavirin tablets are a nucleoside analogue indicated for the treatment of chronic hepatitis C (CHC) virus infection in combination with PEGASYS® in patients 5 years of age and older with compensated liver disease not previously treated with interferon alpha, and in adult CHC patients coinfected with HIV (1)

2 DOSAGE AND ADMINISTRATION

- CHC: Ribavirin tablets are administered according to body weight and genotype (2.1)
- CHC with HIV coinfection: 800 mg by mouth daily for a total of 48 weeks, regardless of genotype (2.2)
- Dose reduction or discontinuation is recommended in patients experiencing certain adverse reactions or renal impairment (2.3, 2.4)

3 DOSAGE FORMS AND STRENGTHS

- Ribavirin tablets, USP 200 mg (3)

4 CONTRAINDICATIONS

- Pregnant women and men whose female partners are pregnant (4, 5.1, 8.1)
- Hemoglobinopathies (4)
- Coadministration with didanosine (4, 7.1)

Ribavirin tablets in combination with PEGASYS® are contraindicated in patients with:

- Autoimmune hepatitis (4)
- Hepatic decompensation in cirrhotic patients (4, 5.3)

5 WARNINGS AND PRECAUTIONS

- Birth defects and fetal death with ribavirin: Do not use in pregnancy and for 6 months after treatment. Patients must have a negative pregnancy test prior to therapy, use at least 2 forms of contraception and undergo monthly pregnancy tests (4, 5.1, 8.1)

PEGASYS®/Ribavirin: Patients exhibiting the following conditions should be closely monitored and may require dose reduction or discontinuation of therapy:

- Hemolytic anemia may occur with a significant initial drop in hemoglobin. This may result in worsening cardiac disease leading to fatal or nonfatal myocardial infarctions (5.2, 6.1)
- Risk of hepatic failure and death: Monitor hepatic function during treatment and discontinue treatment for hepatic decompensation (5.3)
- Severe hypersensitivity reactions including urticaria, angioedema, bronchoconstriction, and anaphylaxis, and serious skin reactions such as Stevens-Johnson syndrome (5.4)
- Pulmonary disorders, including pulmonary function impairment and pneumonitis, including fatal cases of pneumonia (5.5)
- Severe depression and suicidal ideation, autoimmune and infectious disorders, suppression of bone marrow function, pancreatitis, and diabetes (5)
- Bone marrow suppression with azathioprine coadministration (5.6)
- Growth impairment with combination therapy in pediatric patients (5.8)

6 ADVERSE REACTIONS

The most common adverse reactions (frequency greater than 40%) in adults receiving combination therapy are fatigue/asthenia, pyrexia, myalgia, and headache. (6.1)
The most common adverse reactions in pediatric subjects were similar to those seen in adults. (6.1)
To report SUSPECTED ADVERSE REACTIONS, contact Aurobindo Pharma USA, Inc. at 1-866-850-2876 or FDA at 1-800-FDA-1088 or www.fda.gov/medwatch.

7 DRUG INTERACTIONS

- Nucleoside analogues: Closely monitor for toxicities. Discontinue nucleoside reverse transcriptase inhibitors or reduce dose or discontinue interferon, ribavirin or both with worsening toxicities (7.1)
- Azathioprine: Concomitant use of azathioprine with ribavirin has been reported to induce severe pancytopenia and may increase the risk of azathioprine-related myelotoxicity (7.3)

8 USE IN SPECIFIC POPULATIONS

- Pediatrics: Safety and efficacy in pediatric patients less than 5 years old have not been established (8.4)
- Renal Impairment: Dose should be reduced in patients with creatinine clearance less than or equal to 50 mL/min (8.7)
- Organ Transplant: Safety and efficacy have not been studied (8.10)

FULL PRESCRIBING INFORMATION

WARNING: RISK OF SERIOUS DISORDERS AND RIBAVIRIN-ASSOCIATED EFFECTS

Ribavirin monotherapy is not effective for the treatment of chronic hepatitis C virus infection and should not be used alone for this indication.
The primary clinical toxicity of ribavirin is hemolytic anemia. The anemia associated with ribavirin therapy may result in worsening of cardiac disease and lead to fatal and nonfatal myocardial infarctions. Patients with a history of significant or unstable cardiac disease should not be treated with ribavirin [see Warnings and Precautions (5.2), Adverse Reactions (6.1), and Dosage and Administration (2.3)].
Significant teratogenic and/or embryocidal effects have been demonstrated in all animal species exposed to ribavirin. In addition, ribavirin has a multiple dose half-life of 12 days, and it may persist in non-plasma compartments for as long as 6 months. Therefore, ribavirin, including ribavirin tablets, are contraindicated in women who are pregnant and in the male partners of women who are pregnant. Extreme care must be taken to avoid pregnancy during therapy and for 6 months after completion of therapy in both female patients and in female partners of male patients who are taking ribavirin therapy. At least two reliable forms of effective contraception must be utilized during treatment and during the 6-month post treatment follow-up period [see Contraindications (4), Warnings and Precautions (5.1), and Use in Specific Populations (8.1)].

1 INDICATIONS AND USAGE

Ribavirin tablets in combination with PEGASYS® (peginterferon alfa-2a) are indicated for the treatment of patients 5 years of age and older with chronic hepatitis C (CHC) virus infection who have compensated liver disease and have not been previously treated with interferon alpha.
The following points should be considered when initiating ribavirin tablets combination therapy with PEGASYS®:

- This indication is based on clinical trials of combination therapy in patients with CHC and compensated liver disease, some of whom had histological evidence of cirrhosis (Child-Pugh class A), and in adult patients with clinically stable HIV disease and CD4 count greater than 100 cells/mm^3.
- This indication is based on achieving undetectable HCV RNA after treatment for 24 or 48 weeks, based on HCV genotype, and maintaining a Sustained Virologic Response (SVR) 24 weeks after the last dose.
- Safety and efficacy data are not available for treatment longer than 48 weeks.
- The safety and efficacy of ribavirin tablets and PEGASYS® therapy have not been established in liver or other organ transplant recipients, patients with decompensated liver disease, or previous non-responders to interferon therapy.
- The safety and efficacy of ribavirin tablets therapy for the treatment of adenovirus, RSV, parainfluenza or influenza infections have not been established. Ribavirin tablets should not be used for these indications. Ribavirin for inhalation has a separate package insert, which should be consulted if ribavirin inhalation therapy is being considered.

2 DOSAGE AND ADMINISTRATION

Ribavirin tablets should be taken with food. Ribavirin tablets should be given in combination with PEGASYS®; it is important to note that ribavirin tablets should never be given as monotherapy. See PEGASYS® Package Insert for all instructions regarding PEGASYS® dosing and administration.

2.1 Chronic Hepatitis C Monoinfection

Adult Patients
The recommended dose of ribavirin tablets is provided in Table 1. The recommended duration of treatment for patients previously untreated with ribavirin and interferon is 24 to 48 weeks.
The daily dose of ribavirin tablets is 800 mg to 1200 mg administered orally in two divided doses. The dose should be individualized to the patient depending on baseline disease characteristics (e.g., genotype), response to therapy, and tolerability of the regimen (see Table 1).

Table 1 PEGASYS® and Ribavirin Tablets Dosing Recommendations
Hepatitis C Virus (HCV) Genotype | PEGASYS® Dose* (once weekly) | Ribavirin Tablets Dose (daily) | Duration
Genotypes 1, 4 | 180 mcg | <75 kg = 1000 mg ≥75 kg = 1200 mg | 48 weeks 48 weeks
Genotypes 2, 3 | 180 mcg | 800 mg | 24 weeks
Genotypes 2 and 3 showed no increased response to treatment beyond 24 weeks (see Table 10).
Data on genotypes 5 and 6 are insufficient for dosing recommendations.
* See PEGASYS® Package Insert for further details on PEGASYS® dosing and administration, including dose modification in patients with renal impairment.

Pediatric Patients
PEGASYS® is administered as 180 mcg/1.73m^2 x BSA once weekly subcutaneously, to a maximum dose of 180 mcg, and should be given in combination with ribavirin. The recommended treatment duration for patients with genotype 2 or 3 is 24 weeks and for other genotypes is 48 weeks.
Ribavirin tablets should be given in combination with PEGASYS®. Ribavirin tablets are available only as a 200 mg tablet and therefore the healthcare provider should determine if this sized tablet can be swallowed by the pediatric patient. The recommended doses for ribavirin tablets are provided in Table 2. Patients who initiate treatment prior to their 18th birthday should maintain pediatric dosing through the completion of therapy.

Table 2 Ribavirin Tablets Dosing Recommendations for Pediatric Patients
Body Weight in kilograms (kg) | Ribavirin Tablets Daily Dose* | Ribavirin Tablets Number of Tablets
23 to 33 | 400 mg/day | 1 x 200 mg tablet A.M. 1 x 200 mg tablet P.M.
34 to 46 | 600 mg/day | 1 x 200 mg tablet A.M. 2 x 200 mg tablets P.M.
47 to 59 | 800 mg/day | 2 x 200 mg tablets A.M. 2 x 200 mg tablets P.M.
60 to 74 | 1000 mg/day | 2 x 200 mg tablets A.M. 3 x 200 mg tablets P.M.
≥75 | 1200 mg/day | 3 x 200 mg tablets A.M. 3 x 200 mg tablets P.M.
*approximately 15 mg/kg/day

2.2 Chronic Hepatitis C with HIV Coinfection

Adult Patients
The recommended dose for treatment of chronic hepatitis C in patients coinfected with HIV is PEGASYS® 180 mcg subcutaneous once weekly and ribavirin tablets 800 mg by mouth daily for a total duration of 48 weeks, regardless of HCV genotype.

2.3 Dose Modifications

Adult and Pediatric Patients
If severe adverse reactions or laboratory abnormalities develop during combination ribavirin tablets/PEGASYS® therapy, the dose should be modified or discontinued, if appropriate, until the adverse reactions abate or decrease in severity. If intolerance persists after dose adjustment, ribavirin tablets/PEGASYS® therapy should be discontinued. Table 3 provides guidelines for dose modifications and discontinuation based on the patient’s hemoglobin concentration and cardiac status.
Ribavirin tablets should be administered with caution to patients with pre-existing cardiac disease. Patients should be assessed before commencement of therapy and should be appropriately monitored during therapy. If there is any deterioration of cardiovascular status, therapy should be stopped [see Warnings and Precautions (5.2)].

Table 3 Ribavirin Tablets Dose Modification Guidelines in Adults and Pediatrics
Body weight in kilograms (kg) | Laboratory Values
Body weight in kilograms (kg) | Hemoglobin <10 g/dL in patients with no cardiac disease, or Decrease in hemoglobin of ≥2 g/dL during any 4 week period in patients with history of stable cardiac disease | Hemoglobin <8.5 g/dL in patients with no cardiac disease, or Hemoglobin <12 g/dL despite 4 weeks at reduced dose in patients with history of stable cardiac disease
Adult Patients older than 18 years of age
Any weight | 1 x 200 mg tablet A.M. 2 x 200 mg tablets P.M. | Discontinue ribavirin tablets
Pediatric Patients 5 to 18 years of age
23 to 33 kg | 1 x 200 mg tablet A.M. | Discontinue ribavirin tablets
34 to 46 kg | 1 x 200 mg tablet A.M. 1 x 200 mg tablet P.M. | Discontinue ribavirin tablets
47 to 59 kg | 1 x 200 mg tablet A.M. 1 x 200 mg tablet P.M. | Discontinue ribavirin tablets
60 to 74 kg | 1 x 200 mg tablet A.M. 2 x 200 mg tablets P.M. | Discontinue ribavirin tablets
≥75 kg | 1 x 200 mg tablet A.M. 2 x 200 mg tablets P.M. | Discontinue ribavirin tablets

The guidelines for ribavirin tablets dose modifications outlined in this table also apply to laboratory abnormalities or adverse reactions other than decreases in hemoglobin values.
Adult Patients
Once ribavirin tablets have been withheld due to either a laboratory abnormality or clinical adverse reaction, an attempt may be made to restart ribavirin tablets at 600 mg daily and further increase the dose to 800 mg daily. However, it is not recommended that ribavirin tablets be increased to the original assigned dose (1000 mg to 1200 mg).
Pediatric Patients
Upon resolution of a laboratory abnormality or clinical adverse reaction, an increase in ribavirin tablets dose to the original dose may be attempted depending upon the physician’s judgment. If ribavirin tablets have been withheld due to a laboratory abnormality or clinical adverse reaction, an attempt may be made to restart ribavirin tablets at one-half the full dose.

2.4 Renal Impairment

The total daily dose of ribavirin tablets should be reduced for patients with creatinine clearance less than or equal to 50 mL/min; and the weekly dose of PEGASYS® should be reduced for creatinine clearance less than 30 mL/min as follows in Table 4 [see Use in Specific Populations (8.7), Pharmacokinetics (12.3), and PEGASYS® Package Insert].

Table 4 Dosage Modification for Renal Impairment
Creatinine Clearance | PEGASYS® Dose (once weekly) | Ribavirin Tablets Dose (daily)
30 to 50 mL/min | 180 mcg | Alternating doses, 200 mg and 400 mg every other day
Less than 30 mL/min | 135 mcg | 200 mg daily
Hemodialysis | 135 mcg | 200 mg daily

The dose of ribavirin tablets should not be further modified in patients with renal impairment. If severe adverse reactions or laboratory abnormalities develop, ribavirin tablets should be discontinued, if appropriate, until the adverse reactions abate or decrease in severity. If intolerance persists after restarting ribavirin tablets, ribavirin tablets/PEGASYS® therapy should be discontinued.
No data are available for pediatric subjects with renal impairment.

2.5 Discontinuation of Dosing

Discontinuation of PEGASYS®/ribavirin tablets therapy should be considered if the patient has failed to demonstrate at least a 2 log10 reduction from baseline in HCV RNA by 12 weeks of therapy, or undetectable HCV RNA levels after 24 weeks of therapy.
PEGASYS®/Ribavirin tablets therapy should be discontinued in patients who develop hepatic decompensation during treatment [see Warnings and Precautions (5.3)].

3 DOSAGE FORMS AND STRENGTHS

Ribavirin is available as a light pink colored, capsule shaped, film-coated tablet for oral administration. Each tablet contains 200 mg of ribavirin.

4 CONTRAINDICATIONS

Ribavirin tablets are contraindicated in:

- Women who are pregnant. Ribavirin tablets may cause fetal harm when administered to a pregnant woman. Ribavirin tablets are contraindicated in women who are or may become pregnant. If this drug is used during pregnancy, or if the patient becomes pregnant while taking this drug, the patient should be apprised of the potential hazard to the fetus [see Warnings and Precautions (5.1), Use in Specific Populations (8.1), and Patient Counseling Information (17)].
- Men whose female partners are pregnant.
- Patients with hemoglobinopathies (e.g., thalassemia major or sickle-cell anemia).
- In combination with didanosine. Reports of fatal hepatic failure, as well as peripheral neuropathy, pancreatitis, and symptomatic hyperlactatemia/lactic acidosis have been reported in clinical trials [see Drug Interactions (7.1)].

Ribavirin tablets and PEGASYS® combination therapy are contraindicated in patients with:

- Autoimmune hepatitis.
- Hepatic decompensation (Child-Pugh score greater than 6; class B and C) in cirrhotic CHC monoinfected patients before treatment [see Warnings and Precautions (5.3)].
- Hepatic decompensation (Child-Pugh score greater than or equal to 6) in cirrhotic CHC patients coinfected with HIV before treatment [see Warnings and Precautions (5.3)].

5 WARNINGS AND PRECAUTIONS

Significant adverse reactions associated with ribavirin/PEGASYS® combination therapy include severe depression and suicidal ideation, hemolytic anemia, suppression of bone marrow function, autoimmune and infectious disorders, ophthalmologic disorders, cerebrovascular disorders, pulmonary dysfunction, colitis, pancreatitis, and diabetes.
The PEGASYS® Package Insert should be reviewed in its entirety for additional safety information prior to initiation of combination treatment.

5.1 Pregnancy

Ribavirin may cause birth defects and/or death of the exposed fetus. Ribavirin has demonstrated significant teratogenic and/or embryocidal effects in all animal species in which adequate studies have been conducted. These effects occurred at doses as low as one twentieth of the recommended human dose of ribavirin.
Ribavirin therapy should not be started unless a report of a negative pregnancy test has been obtained immediately prior to planned initiation of therapy. Extreme care must be taken to avoid pregnancy in female patients and in female partners of male patients. Patients should be instructed to use at least two forms of effective contraception during treatment and for 6 months after treatment has been stopped. Pregnancy testing should occur monthly during ribavirin therapy and for 6 months after therapy has stopped [see Boxed Warning, Contraindications (4), Use in Specific Populations (8.1), and Patient Counseling Information (17)].

5.2 Anemia

The primary toxicity of ribavirin is hemolytic anemia, which was observed in approximately 13% of all ribavirin/PEGASYS®-treated subjects in clinical trials. Anemia associated with ribavirin occurs within 1 to 2 weeks of initiation of therapy. Because the initial drop in hemoglobin may be significant, it is advised that hemoglobin or hematocrit be obtained pretreatment and at week 2 and week 4 of therapy or more frequently if clinically indicated. Patients should then be followed as clinically appropriate. Caution should be exercised in initiating treatment in any patient with baseline risk of severe anemia (e.g., spherocytosis, history of gastrointestinal bleeding) [see Dosage and Administration (2.3)].
Fatal and nonfatal myocardial infarctions have been reported in patients with anemia caused by ribavirin. Patients should be assessed for underlying cardiac disease before initiation of ribavirin therapy. Patients with pre-existing cardiac disease should have electrocardiograms administered before treatment, and should be appropriately monitored during therapy. If there is any deterioration of cardiovascular status, therapy should be suspended or discontinued [see Dosage and Administration (2.3)]. Because cardiac disease may be worsened by drug-induced anemia, patients with a history of significant or unstable cardiac disease should not use ribavirin [see Boxed Warning and Dosage and Administration (2.3)].

5.3 Hepatic Failure

Chronic hepatitis C (CHC) patients with cirrhosis may be at risk of hepatic decompensation and death when treated with alpha interferons, including PEGASYS®. Cirrhotic CHC patients coinfected with HIV receiving highly active antiretroviral therapy (HAART) and interferon alfa-2a with or without ribavirin appear to be at increased risk for the development of hepatic decompensation compared to patients not receiving HAART. In Study NR15961 [see Clinical Studies (14.3)], among 129 CHC/HIV cirrhotic patients receiving HAART, 14 (11%) of these patients across all treatment arms developed hepatic decompensation resulting in 6 deaths. All 14 patients were on NRTIs, including stavudine, didanosine, abacavir, zidovudine, and lamivudine. These small numbers of patients do not permit discrimination between specific NRTIs or the associated risk. During treatment, patients’ clinical status and hepatic function should be closely monitored for signs and symptoms of hepatic decompensation. Treatment with PEGASYS®/ribavirin should be discontinued immediately in patients with hepatic decompensation [see Contraindications (4)].

5.4 Hypersensitivity

Severe acute hypersensitivity reactions (e.g., urticaria, angioedema, bronchoconstriction, and anaphylaxis) have been observed during alpha interferon and ribavirin therapy. If such a reaction occurs, therapy with PEGASYS® and ribavirin should be discontinued immediately and appropriate medical therapy instituted. Serious skin reactions including vesiculobullous eruptions, reactions in the spectrum of Stevens-Johnson syndrome (erythema multiforme major) with varying degrees of skin and mucosal involvement and exfoliative dermatitis (erythroderma) have been reported in patients receiving PEGASYS® with and without ribavirin. Patients developing signs or symptoms of severe skin reactions must discontinue therapy [see Adverse Reactions (6.2)].

5.5 Pulmonary Disorders

Dyspnea, pulmonary infiltrates, pneumonitis, pulmonary hypertension, and pneumonia have been reported during therapy with ribavirin and interferon. Occasional cases of fatal pneumonia have occurred. In addition, sarcoidosis or the exacerbation of sarcoidosis has been reported. If there is evidence of pulmonary infiltrates or pulmonary function impairment, patients should be closely monitored and, if appropriate, combination ribavirin/PEGASYS® treatment should be discontinued.

5.6 Bone Marrow Suppression

Pancytopenia (marked decreases in RBCs, neutrophils and platelets) and bone marrow suppression have been reported in the literature to occur within 3 to 7 weeks after the concomitant administration of pegylated interferon/ribavirin and azathioprine. In this limited number of patients (n=8), myelotoxicity was reversible within 4 to 6 weeks upon withdrawal of both HCV antiviral therapy and concomitant azathioprine and did not recur upon reintroduction of either treatment alone. PEGASYS®, ribavirin, and azathioprine should be discontinued for pancytopenia, and pegylated interferon/ribavirin should not be re-introduced with concomitant azathioprine [see Drug Interactions (7.3)].

5.7 Pancreatitis

Ribavirin and PEGASYS® therapy should be suspended in patients with signs and symptoms of pancreatitis, and discontinued in patients with confirmed pancreatitis.

5.8 Impact on Growth in Pediatric Patients

During combination therapy for up to 48 weeks with PEGASYS® plus ribavirin, growth inhibition was observed in pediatric subjects 5 to 17 years of age. Decreases in weight for age z-score and height for age z-score up to 48 weeks of therapy compared with baseline were observed. At 2 years post-treatment, 16% of pediatric subjects were more than 15 percentiles below their baseline weight curve and 11% were more than 15 percentiles below their baseline height curve.
The available longer term data on subjects who were followed up to 6 years post-treatment are too limited to determine the risk of reduced adult height in some patients [see Clinical Studies Experience (6.1)].

5.9 Laboratory Tests

Before beginning PEGASYS®/ribavirin combination therapy, standard hematological and biochemical laboratory tests are recommended for all patients. Pregnancy screening for women of childbearing potential must be performed. Patients who have pre-existing cardiac abnormalities should have electrocardiograms administered before treatment with PEGASYS®/ribavirin.
After initiation of therapy, hematological tests should be performed at 2 weeks and 4 weeks and biochemical tests should be performed at 4 weeks. Additional testing should be performed periodically during therapy. In adult clinical studies, the CBC (including hemoglobin level and white blood cell and platelet counts) and chemistries (including liver function tests and uric acid) were measured at 1, 2, 4, 6, and 8 weeks, and then every 4 to 6 weeks or more frequently if abnormalities were found. In the pediatric clinical trial, hematological and chemistry assessments were at 1, 3, 5, and 8 weeks, then every 4 weeks. Thyroid stimulating hormone (TSH) was measured every 12 weeks. Monthly pregnancy testing should be performed during combination therapy and for 6 months after discontinuing therapy.
The entrance criteria used for the clinical studies of ribavirin and PEGASYS® may be considered as a guideline to acceptable baseline values for initiation of treatment:

- Platelet count greater than or equal to 90,000 cells/mm^3 (as low as 75,000 cells/mm^3 in HCV patients with cirrhosis or 70,000 cells/mm^3 in patients with CHC and HIV)
- Absolute neutrophil count (ANC) greater than or equal to 1500 cells/mm^3
- TSH and T4 within normal limits or adequately controlled thyroid function
- CD4+ cell count greater than or equal to 200 cells/mm^3 or CD4+ cell count greater than or equal to 100 cells/mm^3 but less than 200 cells/mm^3 and HIV-1 RNA less than 5,000 copies/mL in patients coinfected with HIV
- Hemoglobin greater than or equal to 12 g/dL for women and greater than or equal to 13 g/dL for men in CHC monoinfected patients
- Hemoglobin greater than or equal to 11 g/dL for women and greater than or equal to 12 g/dL for men in patients with CHC and HIV

6 ADVERSE REACTIONS

PEGASYS® in combination with ribavirin causes a broad variety of serious adverse reactions [see Boxed Warning and Warnings and Precautions (5)]. The most common serious or life-threatening adverse reactions induced or aggravated by ribavirin/PEGASYS® include depression, suicide, relapse of drug abuse/overdose, and bacterial infections each occurring at a frequency of less than 1%. Hepatic decompensation occurred in 2% (10/574) CHC/HIV patients [see Warnings and Precautions (5.3)].

6.1 Clinical Studies Experience

Because clinical trials are conducted under widely varying conditions, adverse reaction rates observed in the clinical trials of a drug cannot be directly compared to rates in the clinical trials of another drug and may not reflect the rates observed in clinical practice.

Adult Patients
In the pivotal registration trials NV15801 and NV15942, 886 patients received ribavirin for 48 weeks at doses of 1000/1200 mg based on body weight. In these trials, one or more serious adverse reactions occurred in 10% of CHC monoinfected subjects and in 19% of CHC/HIV subjects receiving PEGASYS® alone or in combination with ribavirin. The most common serious adverse event (3% in CHC and 5% in CHC/HIV) was bacterial infection (e.g., sepsis, osteomyelitis, endocarditis, pyelonephritis, pneumonia).
Other serious adverse reactions occurred at a frequency of less than 1% and included: suicide, suicidal ideation, psychosis, aggression, anxiety, drug abuse and drug overdose, angina, hepatic dysfunction, fatty liver, cholangitis, arrhythmia, diabetes mellitus, autoimmune phenomena (e.g., hyperthyroidism, hypothyroidism, sarcoidosis, systemic lupus erythematosus, rheumatoid arthritis), peripheral neuropathy, aplastic anemia, peptic ulcer, gastrointestinal bleeding, pancreatitis, colitis, corneal ulcer, pulmonary embolism, coma, myositis, cerebral hemorrhage, thrombotic thrombocytopenic purpura, psychotic disorder, and hallucination.
The percentage of patients in clinical trials who experienced one or more adverse events was 98%. The most commonly reported adverse reactions were psychiatric reactions, including depression, insomnia, irritability, anxiety, and flu-like symptoms such as fatigue, pyrexia, myalgia, headache and rigors. Other common reactions were anorexia, nausea and vomiting, diarrhea, arthralgias, injection site reactions, alopecia, and pruritus. Table 5 shows rates of adverse events occurring in greater than or equal to 5% of subjects receiving pegylated interferon and ribavirin combination therapy in the CHC Clinical Trial, NV15801.
Ten percent of CHC monoinfected patients receiving 48 weeks of therapy with PEGASYS® in combination with ribavirin discontinued therapy; 16% of CHC/HIV coinfected patients discontinued therapy. The most common reasons for discontinuation of therapy were psychiatric, flu-like syndrome (e.g., lethargy, fatigue, headache), dermatologic and gastrointestinal disorders, and laboratory abnormalities (thrombocytopenia, neutropenia, and anemia).
Overall 39% of patients with CHC or CHC/HIV required modification of PEGASYS® and/or ribavirin therapy. The most common reason for dose modification of PEGASYS® in CHC and CHC/HIV patients was for laboratory abnormalities; neutropenia (20% and 27%, respectively) and thrombocytopenia (4% and 6%, respectively). The most common reason for dose modification of ribavirin in CHC and CHC/HIV patients was anemia (22% and 16%, respectively).
PEGASYS® dose was reduced in 12% of patients receiving 1000 mg to 1200 mg ribavirin for 48 weeks and in 7% of patients receiving 800 mg ribavirin for 24 weeks. Ribavirin dose was reduced in 21% of patients receiving 1000 mg to 1200 mg ribavirin for 48 weeks and in 12% of patients receiving 800 mg ribavirin for 24 weeks.
Chronic hepatitis C monoinfected patients treated for 24 weeks with PEGASYS® and 800 mg ribavirin were observed to have lower incidence of serious adverse events (3% vs. 10%), hemoglobin less than 10 g/dL (3% vs. 15%), dose modification of PEGASYS®(30% vs. 36%) and ribavirin (19% vs. 38%), and of withdrawal from treatment (5% vs. 15%) compared to patients treated for 48 weeks with PEGASYS® and 1000 mg or 1200 mg ribavirin. On the other hand, the overall incidence of adverse events appeared to be similar in the two treatment groups.

Table 5 Adverse Reactions Occurring in Greater Than or Equal to 5% of Patients in Chronic Hepatitis C Clinical Trials (Study NV15801)
Body System | CHC Combination Therapy Study NV15801
Body System | PEGASYS® 180 mcg + 1000 mg or 1200 mg Ribavirin Tablets 48 weeks | Interferon alfa-2b + 1000 mg or 1200 mg REBETOL® 48 weeks
Body System | N=451 | N=443
Body System | % | %
Application Site Disorders Injection site reaction | 23 | 16
Endocrine Disorders Hypothyroidism | 4 | 5
Flu-like Symptoms and Signs Fatigue/Asthenia Pyrexia Rigors Pain | 65 41 25 10 | 68 55 37 9
Gastrointestinal Nausea/Vomiting Diarrhea Abdominal pain Dry mouth Dyspepsia | 25 11 8 4 6 | 29 10 9 7 5
Hematologic* Lymphopenia Anemia Neutropenia Thrombocytopenia | 14 11 27 5 | 12 11 8 <1
Metabolic and Nutritional Anorexia Weight decrease | 24 10 | 26 10
Musculoskeletal, Connective Tissue and Bone Myalgia Arthralgia Back pain | 40 22 5 | 49 23 5
Neurological Headache Dizziness (excluding vertigo) Memory impairment | 43 14 6 | 49 14 5
Psychiatric Irritability/Anxiety/Nervousness Insomnia Depression Concentration impairment Mood alteration | 33 30 20 10 5 | 38 37 28 13 6
Resistance Mechanism Disorders Overall | 12 | 10
Respiratory, Thoracic and Mediastinal Dyspnea Cough Dyspnea exertional | 13 10 4 | 14 7 7
Skin and Subcutaneous Tissue Alopecia Pruritus Dermatitis Dry skin Rash Sweating increased Eczema | 28 19 16 10 8 6 5 | 33 18 13 13 5 5 4
Visual Disorders Vision blurred | 5 | 2
* Severe hematologic abnormalities (lymphocyte less than 500 cells/mm^3; hemoglobin less than 10 g/dL; neutrophil less than 750 cells/mm^3; platelet less than 50,000 cells/mm^3).

Pediatric Patients

In a clinical trial with 114 pediatric subjects (5 to 17 years of age) treated with PEGASYS® alone or in combination with ribavirin, dose modifications were required in approximately one-third of subjects, most commonly for neutropenia and anemia. In general, the safety profile observed in pediatric subjects was similar to that seen in adults. In the pediatric study, the most common adverse events in subjects treated with combination therapy PEGASYS® and ribavirin for up to 48 weeks were influenza-like illness (91%), upper respiratory tract infection (60%), headache (64%), gastrointestinal disorder (56%), skin disorder (47%), and injection-site reaction (45%). Seven subjects receiving combination PEGASYS® and ribavirin treatment for 48 weeks discontinued therapy for safety reasons (depression, psychiatric evaluation abnormal, transient blindness, retinal exudates, hyperglycemia, type 1 diabetes mellitus, and anemia). Severe adverse events were reported in 2 subjects in the PEGASYS® plus ribavirin combination therapy group (hyperglycemia and cholecystectomy).

Table 6 Percentage of Pediatric Subjects with Adverse Reactions* During First 24 Weeks of Treatment by Treatment Group and for 24 Weeks Post-treatment (in at Least 10% of Subjects)
 | Study NV17424
System Organ Class | PEGASYS® 180 mcg/1.73 m² x BSA + Ribavirin 15 mg/kg (N=55) | PEGASYS® 180 mcg/1.73 m² x BSA + Placebo** (N=59)
 | % | %
General disorders and administration site conditions
Influenza like illness | 91 | 81
Injection site reaction | 44 | 42
Fatigue | 25 | 20
Irritability | 24 | 14
Gastrointestinal disorders
Gastrointestinal disorder | 49 | 44
Nervous system disorders
Headache | 51 | 39
Skin and subcutaneous tissue disorders
Rash | 15 | 10
Pruritus | 11 | 12
Musculoskeletal, connective tissue and bone disorders
Musculoskeletal pain | 35 | 29
Psychiatric disorders
Insomnia | 9 | 12
Metabolism and nutrition disorders
Decreased appetite | 11 | 14
* Displayed adverse drug reactions include all grades of reported adverse clinical events considered possibly, probably, or definitely related to study drug.
** Subjects in the PEGASYS® plus placebo arm who did not achieve undetectable viral load at week 24 switched to combination treatment thereafter. Therefore, only the first 24 weeks are presented for the comparison of combination therapy with monotherapy.

In pediatric subjects randomized to combination therapy, the incidence of most adverse reactions was similar for the entire treatment period (up to 48 weeks plus 24 weeks follow-up) in comparison to the first 24 weeks, and increased only slightly for headache, gastrointestinal disorder, irritability and rash. The majority of adverse reactions occurred in the first 24 weeks of treatment.
Growth Inhibition in Pediatric Subjects [see Warnings and Precautions (5.8)].
Pediatric subjects treated with PEGASYS® plus ribavirin combination therapy showed a delay in weight and height increases with up to 48 weeks of therapy compared with baseline. Both weight for age and height for age z-scores as well as the percentiles of the normative population for subject weight and height decreased during treatment. At the end of 2 years follow-up after treatment, most subjects had returned to baseline normative curve percentiles for weight (64th mean percentile at baseline, 60 th mean percentile at 2 years post-treatment) and height (54th mean percentile at baseline, 56 th mean percentile at 2 years post-treatment). At the end of treatment, 43% (23 of 53) of subjects experienced a weight percentile decrease of more than 15 percentiles, and 25% (13 of 53) experienced a height percentile decrease of more than 15 percentiles on the normative growth curves. At 2 years post-treatment, 16% (6 of 38) of subjects were more than 15 percentiles below their baseline weight curve and 11% (4 of 38) were more than 15 percentiles below their baseline height curve.
Thirty-eight of the 114 subjects enrolled in the long-term follow-up study, extending up to 6 years post-treatment. For most subjects, post-treatment recovery in growth at 2 years post-treatment was maintained to 6 years post-treatment.
Common Adverse Reactions in CHC with HIV Coinfection (Adults)
The adverse event profile of coinfected patients treated with PEGASYS®/ribavirin in Study NR15961 was generally similar to that shown for monoinfected patients in Study NV15801 (Table 5). Events occurring more frequently in coinfected patients were neutropenia (40%), anemia (14%), thrombocytopenia (8%), weight decrease (16%), and mood alteration (9%).
Laboratory Test Abnormalities

Adult Patients

Anemia due to hemolysis is the most significant toxicity of ribavirin therapy. Anemia (hemoglobin less than 10 g/dL) was observed in 13% of all ribavirin and PEGASYS® combination-treated patients in clinical trials. The maximum drop in hemoglobin occurred during the first 8 weeks of initiation of ribavirin therapy [see Dosage and Administration (2.3)].

Table 7 Selected Laboratory Abnormalities During Treatment with Ribavirin in Combination With Either PEGASYS® or Interferon alfa-2b
Laboratory Parameter | PEGASYS®+ Ribavirin 1000/1200 mg 48 wks | Interferon alfa-2b + Ribavirin 1000/1200 mg 48 wks
 | (N=887) | (N=443)
Neutrophils (cells/mm^3)
1,000 <1,500 | 34% | 38%
500 <1,000 | 49% | 21%
<500 | 5% | 1%
Platelets (cells/mm^3)
50,000 to <75,000 | 11% | 4%
20,000 to <50,000 | 5% | < 1%
<20,000 | 0 | 0
Hemoglobin (g/dL)
8.5 to 9.9 | 11% | 11%
<8.5 | 2% | < 1%

Pediatric Patients

Decreases in hemoglobin, neutrophils and platelets may require dose reduction or permanent discontinuation from treatment [see Dosage and Administration (2.4)]. Most laboratory abnormalities noted during the clinical trial returned to baseline levels shortly after discontinuation of treatment.

Table 8 Selected Hematologic Abnormalities During First 24 Weeks of Treatment by Treatment Group in Previously Untreated Pediatric Subjects
Laboratory Parameter | PEGASYS® 180 mcg/1.73 m² x BSA + Ribavirin 15 mg/kg (N=55) | PEGASYS® 180 mcg/1.73 m² x BSA + Placebo* (N=59)
Neutrophils (cells/mm^3)
1,000 to <1,500 | 31% | 39%
750 to <1,000 | 27% | 17%
500 to <750 | 25% | 15%
<500 | 7% | 5%
Platelets (cells/mm^3)
75,000 to <100,000 | 4% | 2%
50,000 to <75,000 | 0% | 2%
<50,000 | 0% | 0%
Hemoglobin (g/dL)
8.5 to <10 | 7% | 3%
<8.5 | 0% | 0%
* Subjects in the PEGASYS® plus placebo arm who did not achieve undetectable viral load at week 24 switched to combination treatment thereafter. Therefore, only the first 24 weeks are presented for the comparison of combination therapy with monotherapy.

In patients randomized to combination therapy, the incidence of abnormalities during the entire treatment phase (up to 48 weeks plus 24 weeks follow-up) in comparison to the first 24 weeks increased slightly for neutrophils between 500 and 1,000 cells/mm³ and hemoglobin values between 8.5 and 10 g/dL. The majority of hematologic abnormalities occurred in the first 24 weeks of treatment.

6.2 Postmarketing Experience

The following adverse reactions have been identified and reported during post-approval use of PEGASYS®/ribavirin combination therapy. Because these reactions are reported voluntarily from a population of uncertain size, it is not always possible to reliably estimate their frequency or establish a causal relationship to drug exposure.
Blood and Lymphatic System disorders
Pure red cell aplasia
Ear and Labyrinth disorders
Hearing impairment, hearing loss
Eye disorders
Serous retinal detachment
Immune disorders
Liver and renal graft rejection
Metabolism and Nutrition disorders
Dehydration
Skin and Subcutaneous Tissue disorders
Stevens-Johnson syndrome (SJS)
Toxic epidermal necrolysis (TEN)

7 DRUG INTERACTIONS

Results from a pharmacokinetic sub-study demonstrated no pharmacokinetic interaction between PEGASYS® (peginterferon alfa-2a) and ribavirin.

7.1 Nucleoside Reverse Transcriptase Inhibitors (NRTIs)

In vitro data indicate ribavirin reduces phosphorylation of lamivudine, stavudine, and zidovudine. However, no pharmacokinetic (e.g., plasma concentrations or intracellular triphosphorylated active metabolite concentrations) or pharmacodynamic (e.g., loss of HIV/HCV virologic suppression) interaction was observed when ribavirin and lamivudine (n=18), stavudine (n=10), or zidovudine (n=6) were coadministered as part of a multi-drug regimen to HCV/HIV coinfected patients.
In Study NR15961 among the CHC/HIV coinfected cirrhotic patients receiving NRTIs, cases of hepatic decompensation (some fatal) were observed [see Warnings and Precautions (5.3)].
Patients receiving PEGASYS®/ribavirin and NRTIs should be closely monitored for treatment-associated toxicities. Physicians should refer to prescribing information for the respective NRTIs for guidance regarding toxicity management. In addition, dose reduction or discontinuation of PEGASYS®, ribavirin or both should also be considered if worsening toxicities are observed, including hepatic decompensation (e.g., Child-Pugh greater than or equal to 6) [see Warnings and Precautions (5.3) and Dosage and Administration (2.3)].
Didanosine
Coadministration of ribavirin and didanosine is contraindicated. Didanosine or its active metabolite (dideoxyadenosine 5’-triphosphate) concentrations are increased when didanosine is coadministered with ribavirin, which could cause or worsen clinical toxicities. Reports of fatal hepatic failure as well as peripheral neuropathy, pancreatitis, and symptomatic hyperlactatemia/lactic acidosis have been reported in clinical trials [see Contraindications (4)].
Zidovudine
In Study NR15961, patients who were administered zidovudine in combination with PEGASYS®/ribavirin developed severe neutropenia (ANC less than 500) and severe anemia (hemoglobin less than 8 g/dL) more frequently than similar patients not receiving zidovudine (neutropenia 15% vs. 9%) (anemia 5% vs. 1%). Discontinuation of zidovudine should be considered as medically appropriate.

7.2 Drugs Metabolized by Cytochrome P450

In vitro studies indicate that ribavirin does not inhibit CYP 2C9, CYP 2C19, CYP 2D6 or CYP 3A4.

7.3 Azathioprine

The use of ribavirin to treat chronic hepatitis C in patients receiving azathioprine has been reported to induce severe pancytopenia and may increase the risk of azathioprine-related myelotoxicity. Inosine monophosphate dehydrogenase (IMDH) is required for one of the metabolic pathways of azathioprine. Ribavirin is known to inhibit IMDH, thereby leading to accumulation of an azathioprine metabolite, 6-methylthioinosine monophosphate (6-MTITP), which is associated with myelotoxicity (neutropenia, thrombocytopenia, and anemia). Patients receiving azathioprine with ribavirin should have complete blood counts, including platelet counts, monitored weekly for the first month, twice monthly for the second and third months of treatment, then monthly or more frequently if dosage or other therapy changes are necessary [see Warnings and Precautions (5.6)].

8 USE IN SPECIFIC POPULATIONS

8.1 Pregnancy

Pregnancy: Category X [see Contraindications (4)].
Ribavirin produced significant embryocidal and/or teratogenic effects in all animal species in which adequate studies have been conducted. Malformations of the skull, palate, eye, jaw, limbs, skeleton, and gastrointestinal tract were noted. The incidence and severity of teratogenic effects increased with escalation of the drug dose. Survival of fetuses and offspring was reduced [see Contraindications (4) and Warnings and Precautions (5.1)].
In conventional embryotoxicity/teratogenicity studies in rats and rabbits, observed no-effect dose levels were well below those for proposed clinical use (0.3 mg/kg/day for both the rat and rabbit; approximately 0.06 times the recommended daily human dose of ribavirin). No maternal toxicity or effects on offspring were observed in a peri/postnatal toxicity study in rats dosed orally at up to 1 mg/kg/day (approximately 0.01 times the maximum recommended daily human dose of ribavirin).
Treatment and Post-Treatment: Potential Risk to the Fetus

Ribavirin is known to accumulate in intracellular components from where it is cleared very slowly. It is not known whether ribavirin is contained in sperm, and if so, will exert a potential teratogenic effect upon fertilization of the ova. However, because of the potential human teratogenic effects of ribavirin, male patients should be advised to take every precaution to avoid risk of pregnancy for their female partners.
Ribavirin should not be used by pregnant women or by men whose female partners are pregnant. Female patients of childbearing potential and male patients with female partners of childbearing potential should not receive ribavirin unless the patient and his/her partner are using effective contraception (two reliable forms) during therapy and for 6 months post therapy [see Contraindications (4)].

8.3 Nursing Mothers

It is not known whether ribavirin is excreted in human milk. Because many drugs are excreted in human milk and to avoid any potential for serious adverse reactions in nursing infants from ribavirin, a decision should be made either to discontinue nursing or therapy with ribavirin, based on the importance of the therapy to the mother.

8.4 Pediatric Use

Pharmacokinetic evaluations in pediatric patients have not been performed.
Safety and effectiveness of ribavirin have not been established in patients below the age of 5 years.

8.5 Geriatric Use

Clinical studies of ribavirin and PEGASYS® did not include sufficient numbers of subjects aged 65 or over to determine whether they respond differently from younger subjects. Specific pharmacokinetic evaluations for ribavirin in the elderly have not been performed. The risk of toxic reactions to this drug may be greater in patients with impaired renal function. The dose of ribavirin should be reduced in patients with creatinine clearance less than or equal to 50 mL/min; and the dose of PEGASYS® should be reduced in patients with creatinine clearance less than 30 mL/min [see Dosage and Administration (2.4); Use in Specific Populations (8.7)].

8.6 Race

A pharmacokinetic study in 42 subjects demonstrated there is no clinically significant difference in ribavirin pharmacokinetics among Black (n=14), Hispanic (n=13) and Caucasian (n=15) subjects.

8.7 Renal Impairment

Renal function should be evaluated in all patients prior to initiation of ribavirin by estimating the patient’s creatinine clearance.
A clinical trial evaluated treatment with ribavirin and PEGASYS® in 50 CHC subjects with moderate (creatinine clearance 30 to 50 mL/min) or severe (creatinine clearance less than 30 mL/min) renal impairment or end stage renal disease (ESRD) requiring chronic hemodialysis (HD). In 18 subjects with ESRD receiving chronic HD, ribavirin was administered at a dose of 200 mg daily with no apparent difference in the adverse event profile in comparison to subjects with normal renal function. Dose reductions and temporary interruptions of ribavirin (due to ribavirin-related adverse reactions, mainly anemia) were observed in up to one-third ESRD/HD subjects during treatment; and only one-third of these subjects received ribavirin for 48 weeks. Ribavirin plasma exposures were approximately 20% lower in subjects with ESRD on HD compared to subjects with normal renal function receiving the standard 1000/1200 mg ribavirin daily dose.
Subjects with moderate (n=17) or severe (n=14) renal impairment did not tolerate 600 mg or 400 mg daily doses of ribavirin, respectively, due to ribavirin-related adverse reactions, mainly anemia, and exhibited 20% to 30% higher ribavirin plasma exposures (despite frequent dose modifications) compared to subjects with normal renal function (creatinine clearance greater than 80 mL/min) receiving the standard dose of ribavirin. Discontinuation rates were higher in subjects with severe renal impairment compared to that observed in subjects with moderate renal impairment or normal renal function. Pharmacokinetic modeling and simulation indicate that a dose of 200 mg daily in patients with severe renal impairment and a dose of 200 mg daily alternating with 400 mg the following day in patients with moderate renal impairment will provide plasma ribavirin exposure similar to patients with normal renal function receiving the approved regimen of ribavirin. These doses have not been studied in patients [see Dosage and Administration (2.4), and Clinical Pharmacology (12.3)].
Based on the pharmacokinetic and safety results from this trial, patients with creatinine clearance less than or equal to 50 mL/min should receive a reduced dose of ribavirin; and patients with creatinine clearance less than 30 mL/min should receive a reduced dose of PEGASYS®. The clinical and hematologic status of patients with creatinine clearance less than or equal to 50 mL/min receiving ribavirin should be carefully monitored. Patients with clinically significant laboratory abnormalities or adverse reactions which are persistently severe or worsening should have therapy withdrawn [see Dosage and Administration (2.4), Clinical Pharmacology (12.3), and PEGASYS® Package Insert].

8.8 Hepatic Impairment

The effect of hepatic impairment on the pharmacokinetics of ribavirin following administration of ribavirin has not been evaluated. The clinical trials of ribavirin were restricted to patients with Child-Pugh class A disease.

8.9 Gender

No clinically significant differences in the pharmacokinetics of ribavirin were observed between male and female subjects.
Ribavirin pharmacokinetics, when corrected for weight, are similar in male and female patients.

8.10 Organ Transplant Recipients

The safety and efficacy of PEGASYS® and ribavirin treatment have not been established in patients with liver and other transplantations. As with other alpha interferons, liver and renal graft rejections have been reported on PEGASYS®, alone or in combination with ribavirin [see Adverse Reactions (6.2)].

10 OVERDOSAGE

No cases of overdose with ribavirin have been reported in clinical trials. Hypocalcemia and hypomagnesemia have been observed in persons administered greater than the recommended dosage of ribavirin. In most of these cases, ribavirin was administered intravenously at dosages up to and in some cases exceeding four times the recommended maximum oral daily dose.

11 DESCRIPTION

Ribavirin, is a nucleoside analogue with antiviral activity. The chemical name of ribavirin is 1-β-D-ribofuranosyl-1H-1,2,4-triazole-3-carboxamide and has the following structural formula:

The molecular formula of ribavirin is C8H12N4O5 and the molecular weight is 244.2. Ribavirin USP is a white crystalline powder. It is freely soluble in water and slightly soluble in anhydrous alcohol.
Ribavirin USP is available as a light pink colored, capsule shaped, film-coated tablet for oral administration. Each tablet contains 200 mg of ribavirin USP and the following inactive ingredients: microcrystalline cellulose, pregelatinised starch (maize), sodium starch glycolate, povidone (Kollidon 30), colloidal silicon dioxide, magnesium stearate, ethyl cellulose, triacetin, hypromellose, iron oxide red, titanium dioxide, and yellow iron oxide.

12 CLINICAL PHARMACOLOGY

12.1 Mechanism of Action

Ribavirin is an antiviral drug [see Microbiology (12.4)].

12.3 Pharmacokinetics

Multiple dose ribavirin pharmacokinetic data are available for HCV patients who received ribavirin in combination with peginterferon alfa-2a. Following administration of 1200 mg/day with food for 12 weeks mean±SD (n=39; body weight greater than 75 kg) AUC0-12 hr was 25,361±7110 ng·hr/mL and Cmax was 2748±818 ng/mL. The average time to reach Cmax was 2 hours. Trough ribavirin plasma concentrations following 12 weeks of dosing with food were 1662±545 ng/mL in HCV infected patients who received 800 mg/day (n=89), and 2112±810 ng/mL in patients who received 1200 mg/day (n=75; body weight greater than 75 kg).
The terminal half-life of ribavirin following administration of a single oral dose of ribavirin is about 120 to 170 hours. The total apparent clearance following administration of a single oral dose of ribavirin is about 26 L/h. There is extensive accumulation of ribavirin after multiple dosing (twice daily) such that the Cmax at steady state was four-fold higher than that of a single dose.
Effect of Food on Absorption of Ribavirin
Bioavailability of a single oral dose of ribavirin was increased by coadministration with a high-fat meal. The absorption was slowed (Tmax was doubled) and the AUC0-192 h and Cmax increased by 42% and 66%, respectively, when ribavirin was taken with a high-fat meal compared with fasting conditions [see Dosage and Administration (2) and Patient Counseling Information (17)].
Elimination and Metabolism
The contribution of renal and hepatic pathways to ribavirin elimination after administration of ribavirin is not known. In vitro studies indicate that ribavirin is not a substrate of CYP450 enzymes.
Renal Impairment
A clinical trial evaluated 50 CHC subjects with either moderate (creatinine clearance 30 to 50 mL/min) or severe (creatinine clearance less than 30 mL/min) renal impairment or end stage renal disease (ESRD) requiring chronic hemodialysis (HD). The apparent clearance of ribavirin was reduced in subjects with creatinine clearance less than or equal to 50 mL/min, including subjects with ESRD on HD, exhibiting approximately 30% of the value found in subjects with normal renal function. Pharmacokinetic modeling and simulation indicates that a dose of 200 mg daily in patients with severe renal impairment and a dose of 200 mg daily alternating with 400 mg the following day in patients with moderate renal impairment will provide plasma ribavirin exposures similar to that observed in patients with normal renal function receiving the standard 1000/1200 mg ribavirin daily dose. These doses have not been studied in patients.
In 18 subjects with ESRD receiving chronic HD, ribavirin was administered at a dose of 200 mg daily. Ribavirin plasma exposures in these subjects were approximately 20% lower compared to subjects with normal renal function receiving the standard 1000/1200 mg ribavirin daily dose [see Dosage and Administration (2.4), Use in Specific Populations (8.7)].
Plasma ribavirin is removed by hemodialysis with an extraction ratio of approximately 50%; however, due to the large volume of distribution of ribavirin, plasma exposure is not expected to change with hemodialysis.

12.4 Microbiology

Mechanism of Action
The mechanism by which ribavirin contributes to its antiviral efficacy in the clinic is not fully understood. Ribavirin has direct antiviral activity in tissue culture against many RNA viruses. Ribavirin increases the mutation frequency in the genomes of several RNA viruses and ribavirin triphosphate inhibits HCV polymerase in a biochemical reaction.
Antiviral Activity in Cell Culture
In the stable HCV cell culture model system (HCV replicon), ribavirin inhibited autonomous HCV RNA replication with a 50% effective concentration (EC50) value of 11 to 21 mcM. In the same model, PEG-IFN α-2a also inhibited HCV RNA replication, with an EC50 value of 0.1 to 3 ng/mL. The combination of PEG-IFN α-2a and ribavirin was more effective at inhibiting HCV RNA replication than either agent alone.
Resistance
Different HCV genotypes display considerable clinical variability in their response to PEG-IFN-α and ribavirin therapy. Viral genetic determinants associated with the variable response have not been definitively identified.
Cross-resistance
Cross-resistance between IFN α and ribavirin has not been observed.

13 NONCLINICAL TOXICOLOGY

13.1 Carcinogenesis, Mutagenesis, Impairment of Fertility

Carcinogenesis
In a p53 (+/-) mouse carcinogenicity study up to the maximum tolerated dose of 100 mg/kg/day, ribavirin was not oncogenic. Ribavirin was also not oncogenic in a rat 2-year carcinogenicity study at doses up to the maximum tolerated dose of 60 mg/kg/day. On a body surface area basis, these doses are approximately 0.5 and 0.6 times the maximum recommended daily human dose of ribavirin, respectively.
Mutagenesis
Ribavirin demonstrated mutagenic activity in the in vitro mouse lymphoma assay. No clastogenic activity was observed in an in vivo mouse micronucleus assay at doses up to 2000 mg/kg. However, results from studies published in the literature show clastogenic activity in the in vivo mouse micronucleus assay at oral doses up to 2000 mg/kg. A dominant lethal assay in rats was negative, indicating that if mutations occurred in rats they were not transmitted through male gametes.
Impairment of Fertility
In a fertility study in rats, ribavirin showed a marginal reduction in sperm counts at the dose of 100 mg/kg/day with no effect on fertility. Upon cessation of treatment, total recovery occurred after 1 spermatogenesis cycle. Abnormalities in sperm were observed in studies in mice designed to evaluate the time course and reversibility of ribavirin-induced testicular degeneration at doses of 15 to 150 mg/kg/day (approximately 0.1 to 0.8 times the maximum recommended daily human dose of ribavirin) administered for 3 to 6 months. Upon cessation of treatment, essentially total recovery from ribavirin-induced testicular toxicity was apparent within 1 or 2 spermatogenic cycles.
Female patients of childbearing potential and male patients with female partners of childbearing potential should not receive ribavirin unless the patient and his/her partner are using effective contraception (two reliable forms). Based on a multiple dose half-life (t1/2) of ribavirin of 12 days, effective contraception must be utilized for 6 months post therapy (i.e., 15 half-lives of clearance for ribavirin).
No reproductive toxicology studies have been performed using PEGASYS® in combination with ribavirin. However, peginterferon alfa-2a and ribavirin when administered separately, each has adverse effects on reproduction. It should be assumed that the effects produced by either agent alone would also be caused by the combination of the two agents.

13.2 Animal Toxicology

In a study in rats, it was concluded that dominant lethality was not induced by ribavirin at doses up to 200 mg/kg for 5 days (up to 1.7 times the maximum recommended human dose of ribavirin).
Long-term studies in the mouse and rat (18 to 24 months; dose 20 to 75, and 10 to 40 mg/kg/day, respectively, approximately 0.1 to 0.4 times the maximum daily human dose of ribavirin) have demonstrated a relationship between chronic ribavirin exposure and an increased incidence of vascular lesions (microscopic hemorrhages) in mice. In rats, retinal degeneration occurred in controls, but the incidence was increased in ribavirin-treated rats.

14 CLINICAL STUDIES

14.1 Chronic Hepatitis C Patients

Adult Patients
The safety and effectiveness of PEGASYS® in combination with ribavirin for the treatment of hepatitis C virus infection were assessed in two randomized controlled clinical trials. All patients were adults, had compensated liver disease, detectable hepatitis C virus, liver biopsy diagnosis of chronic hepatitis, and were previously untreated with interferon. Approximately 20% of patients in both studies had compensated cirrhosis (Child-Pugh class A). Patients coinfected with HIV were excluded from these studies.
In Study NV15801, patients were randomized to receive either PEGASYS® 180 mcg subcutaneous once weekly with an oral placebo, PEGASYS® 180 mcg once weekly with ribavirin 1000 mg by mouth (body weight less than 75 kg) or 1200 mg by mouth (body weight greater than or equal to 75 kg) or interferon alfa-2b 3 MIU subcutaneous three times a week plus ribavirin 1000 mg or 1200 mg by mouth. All patients received 48 weeks of therapy followed by 24 weeks of treatment-free follow-up. Ribavirin or placebo treatment assignment was blinded. Sustained virological response was defined as undetectable (less than 50 IU/mL) HCV RNA on or after study week 68. PEGASYS® in combination with ribavirin resulted in a higher SVR compared to PEGASYS® alone or interferon alfa-2b and ribavirin (Table 9). In all treatment arms, patients with viral genotype 1, regardless of viral load, had a lower response rate to PEGASYS® in combination with ribavirin compared to patients with other viral genotypes.

Table 9 Sustained Virologic Response (SVR) to Combination Therapy (Study NV15801)
 | Interferon alfa-2b + Ribavirin 1000 mg or 1200 mg | PEGASYS® + Placebo | PEGASYS® + Ribavirin 1000 mg or 1200 mg
All patients | 197/444 (44%) | 65/224 (29%) | 241/453 (53%)
Genotype 1 | 103/285 (36%) | 29/145 (20%) | 132/298 (44%)
Genotypes 2 to 6 | 94/159 (59%) | 36/79 (46%) | 109/155 (70%)

Difference in overall treatment response (PEGASYS®/ribavirin – Interferon alfa-2b/ribavirin) was 9% (95% CI 2.3, 15.3).
In Study NV15942, all patients received PEGASYS® 180 mcg subcutaneous once weekly and were randomized to treatment for either 24 or 48 weeks and to a ribavirin dose of either 800 mg or 1000 mg/1200 mg (for body weight less than 75 kg/greater than or equal to 75 kg). Assignment to the four treatment arms was stratified by viral genotype and baseline HCV viral titer. Patients with genotype 1 and high viral titer (defined as greater than 2 x 10^6 HCV RNA copies/mL serum) were preferentially assigned to treatment for 48 weeks.
Sustained Virologic Response (SVR) and HCV Genotype
HCV 1 and 4 - Irrespective of baseline viral titer, treatment for 48 weeks with PEGASYS® and 1000 mg or 1200 mg of ribavirin resulted in higher SVR (defined as undetectable HCV RNA at the end of the 24-week treatment-free follow-up period) compared to shorter treatment (24 weeks) and/or 800 mg ribavirin.
HCV 2 and 3 - Irrespective of baseline viral titer, treatment for 24 weeks with PEGASYS® and 800 mg of ribavirin resulted in a similar SVR compared to longer treatment (48 weeks) and/or 1000 mg or 1200 mg of ribavirin (see Table 10).
The numbers of patients with genotype 5 and 6 were too few to allow for meaningful assessment.

Table 10 Sustained Virologic Response as a Function of Genotype (Study NV15942)
 | 24 Weeks Treatment |  | 48 Weeks Treatment
 | PEGASYS® + Ribavirin 800 mg (N=207) | PEGASYS® + Ribavirin 1000 mg or 1200 mg* (N=280) | PEGASYS® + Ribavirin 800 mg (N=361) | PEGASYS® + Ribavirin 1000 mg or 1200 mg* (N=436)
Genotype 1 | 29/101 (29%) | 48/118 (41%) | 99/250 (40%) | 138/271 (51%)
Genotypes 2, 3 | 79/96 (82%) | 116/144 (81%) | 75/99 (76%) | 117/153 (76%)
Genotype 4 | 0/5 (0%) | 7/12 (58%) | 5/8 (63%) | 9/11 (82%)
* 1000 mg for body weight less than 75 kg; 1200 mg for body weight greater than or equal to 75 kg.

Pediatric Patients
Previously untreated pediatric subjects 5 through 17 years of age (55% less than 12 years old) with chronic hepatitis C, compensated liver disease and detectable HCV RNA were treated with ribavirin approximately 15 mg/kg/day plus PEGASYS® 180 mcg/1.73 m^2 x body surface area once weekly for 48 weeks. All subjects were followed for 24 weeks post-treatment. Sustained virological response (SVR) was defined as undetectable (less than 50 IU/mL) HCV RNA on or after study week 68. A total of 114 subjects were randomized to receive either combination treatment of ribavirin plus PEGASYS® or PEGASYS® monotherapy; subjects failing PEGASYS® monotherapy at 24 weeks or later could receive open-label ribavirin plus PEGASYS®. The initial randomized arms were balanced for demographic factors; 55 subjects received initial combination treatment of ribavirin plus PEGASYS® and 59 received PEGASYS® plus placebo; in the overall intent-to-treat population, 45% were female, 80% were Caucasian, and 81% were infected with HCV genotype 1. The SVR results are summarized in Table 11.

Table 11 Sustained Virologic Response (Study NV17424)
 | PEGASYS® 180 mcg/1.73 m^2 x BSA + Ribavirin 15 mg/kg* (N=55) | PEGASYS® 180 mcg/1.73 m^2 x BSA + Placebo* (N=59)
All HCV genotypes** | 29 (53%) | 12 (20%)
HCV genotype 1 | 21/45 (47%) | 8/47 (17%)
HCV non-genotype 1*** | 8/10 (80%) | 4/12 (33%)
*Results indicate undetectable HCV RNA defined as HCV RNA less than 50 IU/mL at 24 weeks post-treatment using the AMPLICOR HCV test v2 **Scheduled treatment duration was 48 weeks regardless of the genotype
***Includes HCV genotypes 2, 3 and others

14.2 Other Treatment Response Predictors

Treatment response rates are lower in patients with poor prognostic factors receiving pegylated interferon alpha therapy. In studies NV15801 and NV15942, treatment response rates were lower in patients older than 40 years (50% vs. 66%), in patients with cirrhosis (47% vs. 59%), in patients weighing over 85 kg (49% vs. 60%), and in patients with genotype 1 with high vs. low viral load (43% vs. 56%). African-American patients had lower response rates compared to Caucasians.
In studies NV15801 and NV15942, lack of early virologic response by 12 weeks (defined as HCV RNA undetectable or greater than 2 log10 lower than baseline) was grounds for discontinuation of treatment. Of patients who lacked an early viral response by 12 weeks and completed a recommended course of therapy despite a protocol-defined option to discontinue therapy, 5/39 (13%) achieved an SVR. Of patients who lacked an early viral response by 24 weeks, 19 completed a full course of therapy and none achieved an SVR.

14.3 Chronic Hepatitis C/HIV Coinfected Patients

In Study NR15961, patients with CHC/HIV were randomized to receive either PEGASYS® 180 mcg subcutaneous once weekly plus an oral placebo, PEGASYS® 180 mcg once weekly plus ribavirin 800 mg by mouth daily or interferon alfa-2a, 3 MIU subcutaneous three times a week plus ribavirin 800 mg by mouth daily. All patients received 48 weeks of therapy and sustained virologic response (SVR) was assessed at 24 weeks of treatment-free follow-up. Ribavirin or placebo treatment assignment was blinded in the PEGASYS® treatment arms. All patients were adults, had compensated liver disease, detectable hepatitis C virus, liver biopsy diagnosis of chronic hepatitis C, and were previously untreated with interferon. Patients also had CD4+ cell count greater than or equal to 200 cells/mm^3 or CD4+ cell count greater than or equal to 100 cells/mm^3 but less than 200 cells/mm^3 and HIV-1 RNA less than 5000 copies/mL, and stable status of HIV. Approximately 15% of patients in the study had cirrhosis. Results are shown in Table 12.

Table 12 Sustained Virologic Response in Patients with Chronic Hepatitis C Coinfected With HIV (Study NR15961)
 | Interferon alfa-2a + Ribavirin 800 mg (N=289) | PEGASYS® + Placebo (N=289) | PEGASYS® + Ribavirin 800 mg (N=290)
All patients | 33 (11%) | 58 (20%) | 116 (40%)
Genotype 1 | 12/171 (7%) | 24/175 (14%) | 51/176 (29%)
Genotypes 2, 3 | 18/89 (20%) | 32/90 (36%) | 59/95 (62%)

Treatment response rates were lower in CHC/HIV patients with poor prognostic factors (including HCV genotype 1, HCV RNA greater than 800,000 IU/mL, and cirrhosis) receiving pegylated interferon alpha therapy.
Of the patients who did not demonstrate either undetectable HCV RNA or at least a 2 log10 reduction from baseline in HCV RNA titer by 12 weeks of PEGASYS® and ribavirin combination therapy, 2% (2/85) achieved an SVR.
In CHC patients with HIV coinfection who received 48 weeks of PEGASYS® alone or in combination with ribavirin treatment, mean and median HIV RNA titers did not increase above baseline during treatment or 24 weeks post-treatment.

16 HOW SUPPLIED/STORAGE AND HANDLING

Ribavirin Tablets USP, 200 mg are light pink colored, capsule shaped, film-coated tablets debossed with ‘F’ on one side and ‘10’ on the other side.
Bottles of 168 NDC 65862-207-68
Bottles of 500 NDC 65862-207-05
Storage and Handling
Store at 20° to 25°C (68° to 77°F); excursions permitted to 15° to 30°C (59° to 86°F) [see USP Controlled Room Temperature]. Keep bottle tightly closed.

17 PATIENT COUNSELING INFORMATION

- See FDA-approved patient labeling (Medication Guide)

Pregnancy
Patients must be informed that ribavirin may cause birth defects and/or death of the exposed fetus. Ribavirin therapy must not be used by women who are pregnant or by men whose female partners are pregnant. Extreme care must be taken to avoid pregnancy in female patients and in female partners of male patients taking ribavirin therapy and for 6 months post therapy. Patients should use two reliable methods of birth control while taking ribavirin therapy and for 6 months post therapy. Ribavirin therapy should not be initiated until a report of a negative pregnancy test has been obtained immediately prior to initiation of therapy. Patients must perform a pregnancy test monthly during therapy and for 6 months post therapy.
Female patients of childbearing potential and male patients with female partners of childbearing potential must be advised of the teratogenic/embryocidal risks and must be instructed to practice effective contraception during ribavirin therapy and for 6 months post therapy. Patients should be advised to notify the healthcare provider immediately in the event of a pregnancy [see Contraindications (4) and Warnings and Precautions (5.1)].
Anemia
The most common adverse event associated with ribavirin is anemia, which may be severe [see Boxed Warning, Warnings and Precautions (5.2) and Adverse Reactions (6.1)]. Patients should be advised that laboratory evaluations are required prior to starting ribavirin therapy and periodically thereafter [see Warnings and Precautions (5.9)]. It is advised that patients be well hydrated, especially during the initial stages of treatment.
Patients who develop dizziness, confusion, somnolence, and fatigue should be cautioned to avoid driving or operating machinery.
Patients should be advised to take ribavirin with food.
Patients should be questioned about prior history of drug abuse before initiating ribavirin/PEGASYS®, as relapse of drug addiction and drug overdoses have been reported in patients treated with interferons.
Patients should be advised not to drink alcohol, as alcohol may exacerbate chronic hepatitis C infection.
Patients should be informed about what to do in the event they miss a dose of ribavirin. The missed doses should be taken as soon as possible during the same day. Patients should not double the next dose. Patients should be advised to call their healthcare provider if they have questions.
Patients should be informed that the effect of PEGASYS®/ribavirin treatment of hepatitis C infection on transmission is not known, and that appropriate precautions to prevent transmission of hepatitis C virus during treatment or in the event of treatment failure should be taken.
Patients should be informed regarding the potential benefits and risks attendant to the use of ribavirin. Instructions on appropriate use should be given, including review of the contents of the enclosed MEDICATION GUIDE, which is not a disclosure of all or possible adverse effects.
Dispense with Medication Guide available at: www.aurobindousa.com/medication-guides
Distributed by:
Aurobindo Pharma USA, Inc.
279 Princeton-Hightstown Road
East Windsor, NJ 08520

Manufactured by:
Aurobindo Pharma Limited
Hyderabad–500 032, India
Revised: 05/2023

Dispense with Medication Guide available at: www.aurobindousa.com/medication-guides

MEDICATION GUIDE

Ribavirin Tablets, USP
(rye" ba vye' rin)
Read this Medication Guide carefully before you start taking ribavirin tablets and read the Medication Guide each time you get more ribavirin tablets. There may be new information. This information does not take the place of talking to your healthcare provider about your medical condition or your treatment.
Also read the Medication Guide for PEGASYS® (peginterferon alfa-2a).
What is the most important information I should know about ribavirin tablets?

1. You should not take ribavirin tablets alone to treat chronic hepatitis C infection. Ribavirin tablets should be used with PEGASYS® to treat chronic hepatitis C infection.

2. Ribavirin tablets may cause you to have a blood problem (hemolytic anemia) that can worsen any heart problems you have, and cause you to have a heart attack or die. Tell your healthcare provider if you have ever had any heart problems. Ribavirin tablets may not be right for you. If you have chest pain while you take ribavirin tablets, get emergency medical attention right away.

3. Ribavirin tablets may cause birth defects or death of your unborn baby. If you are pregnant or your sexual partner is pregnant, do not take ribavirin tablets. You or your sexual partner should not become pregnant while you take ribavirin tablets and for 6 months after treatment is over. You must use two forms of birth control when you take ribavirin tablets and for the 6 months after treatment.

- Females must have a pregnancy test before starting ribavirin tablets, every month while treated with ribavirin tablets, and every month for the 6 months after treatment with ribavirin tablets.
- If you or your female sexual partner becomes pregnant while taking ribavirin tablets or within 6 months after you stop taking ribavirin tablets, tell your healthcare provider right away.

What are ribavirin tablets?
Ribavirin tablets are a prescription medicine used with another medicine called PEGASYS® (peginterferon alfa-2a) to treat chronic (lasting a long time) hepatitis C infection in people 5 years and older whose liver still works normally, and who have not been treated before with a medicine called an interferon alpha. It is not known if ribavirin tablets are safe and will work in children under 5 years of age.
Who should not take ribavirin tablets?
See “What is the most important information I should know about ribavirin tablets?”

Do not take ribavirin tablets if you:

- have certain types of hepatitis caused by your immune system attacking your liver (autoimmune hepatitis)
- have certain blood disorders, such as thalassemia major or sickle-cell anemia (hemoglobinopathies)
- take didanosine (Videx or Videx EC)

Talk to your healthcare provider before starting treatment with ribavirin tablets if you have any of these medical conditions.
What should I tell my healthcare provider before taking ribavirin tablets?
Before you take ribavirin tablets, tell your healthcare provider if you have or have had:

- treatment for hepatitis C that did not work for you
- serious allergic reactions to ribavirin tablets or to any of the ingredients in ribavirin tablets. See the end of this Medication Guide for a list of ingredients.
- breathing problems. Ribavirin tablets may cause or worsen your breathing problems you already have.
- vision problems. Ribavirin tablets may cause eye problems or worsen eye problems you already have. You should have an eye exam before you start treatment with ribavirin tablets.
- certain blood disorders such as anemia
- high blood pressure, heart problems or have had a heart attack. Your healthcare provider should test your blood and heart before you start treatment with ribavirin tablets.
- thyroid problems
- diabetes. Ribavirin tablets and PEGASYS® combination therapy may make your diabetes worse or harder to treat.
- liver problems other than hepatitis C virus infection
- human immunodeficiency virus (HIV) or other immunity problems
- mental health problems, including depression or thoughts of suicide
- kidney problems
- an organ transplant
- drug addiction or abuse
- infection with hepatitis B virus
- any other medical condition
- are breast feeding. It is not known if ribavirin passes into your breast milk. You and your healthcare provider should decide if you will take ribavirin tablets or breastfeed.

Tell your healthcare provider about all the medicines you take, including prescription and non-prescription medicines, vitamins and herbal supplements. Some medicines can cause serious side effects if taken while you also take ribavirin tablets. Some medicines may affect how ribavirin tablets work or ribavirin tablets may affect how your other medicines work.
Especially tell your healthcare provider if you take any medicines to treat HIV, including didanosine (Videx or Videx EC), or if you take azathioprine (Imuran or Azasan).
Know the medicines you take. Keep a list of them to show your healthcare provider or pharmacist when you get a new medicine.
How should I take ribavirin tablets?

- Take ribavirin tablets exactly as your healthcare provider tells you. Your healthcare provider will tell you how much ribavirin tablets to take and when to take them. For children 5 years of age and older your healthcare provider will prescribe the dose of ribavirin tablets based on weight.
- Take ribavirin tablets with food.
- If you miss a dose of ribavirin tablets, take the missed dose as soon as possible during the same day. Do not double the next dose. If you have questions about what to do, call your healthcare provider.
- If you take too much ribavirin tablets, call your healthcare provider or local Poison Control Center right away, or go the nearest hospital emergency room right away.
- Your healthcare provider should do blood tests before you start treatment with ribavirin tablets, at weeks 2 and 4 of treatment, and then as needed to see how well you are tolerating treatment and to check for side effects. Your healthcare provider may change your dose of ribavirin tablets based on blood test results or side effects you may have.
- If you have heart problems, your healthcare provider should check your heart by doing an electrocardiogram before you start treatment with ribavirin tablets, and if needed during treatment.

What should I avoid while taking ribavirin tablets?

- Ribavirin tablets can make you feel tired, dizzy, or confused. You should not drive or operate machinery if you have any of these symptoms.
- Do not drink alcohol, including beer, wine, and liquor. This may make your liver disease worse.

What are the possible side effects of ribavirin tablets?
Ribavirin tablets may cause serious side effects including:
See “What is the most important information I should know about ribavirin tablets?”

- Swelling and irritation of your pancreas (pancreatitis). You may have stomach pain, nausea, vomiting or diarrhea.
- Severe allergic reactions. Symptoms may include hives, wheezing, trouble breathing, chest pain, swelling of your mouth, tongue, or lips, or severe rash.
- Serious breathing problems. Difficulty breathing may be a sign of a serious lung infection (pneumonia) that can lead to death.
- Serious eye problems that may lead to vision loss or blindness.
- Liver problems. Some people may get worsening of liver function. Tell your healthcare provider right away if you have any of these symptoms: stomach bloating, confusion, brown urine, and yellow eyes.
- Severe depression
- Suicidal thoughts and attempts
- Effect on growth in children. Children can experience a delay in weight gain and height increase while being treated with PEGASYS® and ribavirin tablets. Catch-up in growth happens after treatment stops, but some children may not reach the height that they were expected to have before treatment. Talk to your healthcare provider if you are concerned about your child’s growth during treatment with PEGASYS® and ribavirin tablets.

Call your healthcare provider or get medical help right away if you have any of the symptoms listed above. These may be signs of a serious side effect of ribavirin tablets treatment.

Common side effects of ribavirin tablets taken with PEGASYS® include:

- flu-like symptoms-feeling tired, headache, shaking along with high temperature (fever), and muscle or joint aches
- mood changes, feeling irritable, anxiety, and difficulty sleeping
- loss of appetite, nausea, vomiting, and diarrhea
- hair loss
- itching

Tell your healthcare provider about any side effect that bothers you or that does not go away.
These are not all the possible side effects of ribavirin tablets treatment. For more information, ask your healthcare provider or pharmacist.
Call your doctor for medical advice about side effects. You may report side effects to FDA at 1-800-FDA-1088.
You may also report side effects to Aurobindo Pharma USA, Inc. at 1-866-850-2876.
How should I store ribavirin tablets?

- Store ribavirin tablets at 20° to 25°C (68° to 77°F); excursions permitted to 15° to 30°C (59° to 86°F) [see USP Controlled Room Temperature].
- Keep the bottle tightly closed.

Keep ribavirin tablets and all medicines out of the reach of children.
General information about the safe and effective use of ribavirin tablets
It is not known if treatment with ribavirin tablets in combination with PEGASYS® will prevent an infected person from spreading the hepatitis C virus to another person while on treatment.
Medicines are sometimes prescribed for purposes other than those listed in a Medication Guide. Do not use ribavirin tablets for a condition for which it was not prescribed. Do not give ribavirin tablets to other people, even if they have the same symptoms that you have. They may harm them.
This Medication Guide summarizes the most important information about ribavirin tablets. If you would like more information, talk with your healthcare provider. You can ask your healthcare provider or pharmacist for information about ribavirin tablets that is written for healthcare professionals.
What are the ingredients in ribavirin tablets?
Active Ingredient: ribavirin
Inactive Ingredients: microcrystalline cellulose, pregelatinised starch (maize), sodium starch glycolate, povidone (Kollidon 30), colloidal silicon dioxide, magnesium stearate, ethyl cellulose, triacetin, hypromellose, iron oxide red, titanium dioxide, and yellow iron oxide.
This Medication Guide has been approved by the U.S. Food and Drug Administration.
Trademarks are the property of their respective owners.
Distributed by:
Aurobindo Pharma USA, Inc.
279 Princeton-Hightstown Road
East Windsor, NJ 08520

Manufactured by:
Aurobindo Pharma Limited
Hyderabad–500 032, India
Revised: 05/2023

PACKAGE LABEL-PRINCIPAL DISPLAY PANEL - 200 mg (168 Tablet Bottle)

NDC 65862-207-68
Rx only
Ribavirin Tablets, USP
200 mg
PHARMACIST: DISPENSE THE MEDICATION GUIDE
PROVIDED SEPARATELY TO EACH PATIENT.
AUROBINDO 168 Tablets